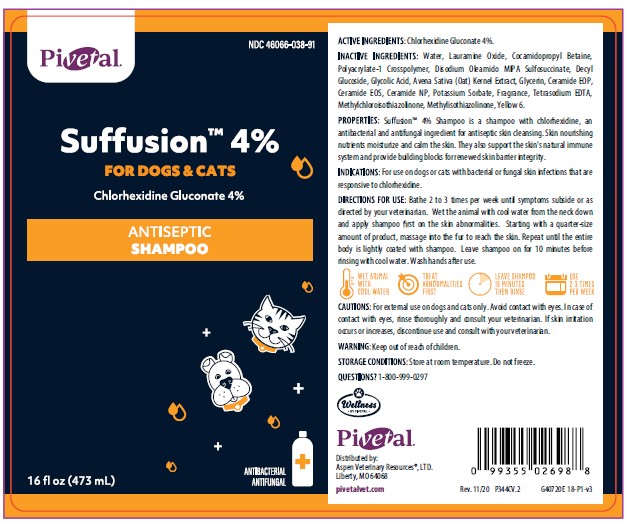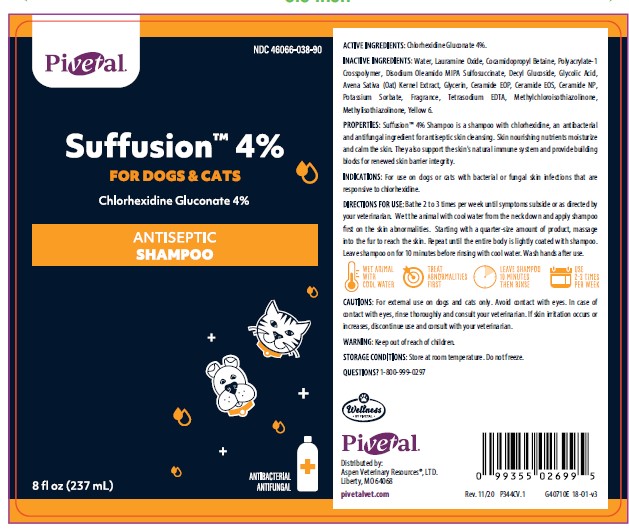 DRUG LABEL: SUFFUSION
NDC: 46066-038 | Form: SHAMPOO
Manufacturer: ASPEN VETERINARY RESOURCES
Category: animal | Type: OTC ANIMAL DRUG LABEL
Date: 20210407

ACTIVE INGREDIENTS: CHLORHEXIDINE GLUCONATE 40 mg/1 mL
INACTIVE INGREDIENTS: WATER; LAURAMINE OXIDE; COCAMIDOPROPYL BETAINE; CARBOMER HOMOPOLYMER, UNSPECIFIED TYPE; DISODIUM OLEAMIDO MIPA-SULFOSUCCINATE; DECYL GLUCOSIDE; GLYCOLIC ACID; AVENANTHRAMIDES; GLYCERIN; CERAMIDE 1; CERAMIDE EOS; CERAMIDE NP; POTASSIUM SORBATE; EDETATE SODIUM; METHYLCHLOROISOTHIAZOLINONE; METHYLISOTHIAZOLINONE

DESCRIPTION

Suffusion™ 4%

FOR DOGS & CATS

Chlorhexidine Gluconate 4%

ANTISEPTIC SHAMPOO

ACTIVE INGREDIENT: Chlorhexidine Gluconate 4%

INACTIVE INGREDIENTS: Water, Lauramine Oxide, Cocamidopropyl Betaine, Polyacrylate-1 Crosspolymer, Disodium Oleamido MIPA Sulfosuccinate, Decyl Glucoside, Glycolic Acid, Avena Sativa (Oat) Kernal Extract, Glycerin, Ceramide EOS, Ceramide EOP, Ceramide NP, Potassium Sorbate, Fragrance, Tetrasodium EDTA, Sodium Chloride, Methylchloroisothiazolinone, Methylisothiazolinone, Yellow 6.

PROPERTIES: Suffusion™ 4% Shampoo is a shampoo with chlorhexidine, an antibacterial and antifungal ingredient for antiseptic skin cleansing. Skin nourishing nutrients moisturiize and calm the skin. They also support the skin's natural immune system and provide building blocks for renewed skin barrier integrity.

INDICATIONS AND USAGE

INDICATIONS: For use on dogs or cats with bacterial or fungal skin infections that are responsive to chlorhexidine.

DIRECTIONS FOR USE: Bathe 2-3 times per week until symptoms subside or as directed by your veterinarian. Wet the animal with cool water from the neck down and apply the shampoo first on the skin abnormalities. Starting with a quarter-size amount of product, massage in the fur to reach the skin. Repeat until the entire body is lightly coated with shampoo. Leave shampoo on for 10 minutes before rinsing with cool water. Wash hands after use.

WARNINGS AND PRECAUTIONS

CAUTIONS: For external use on dogs and cats only. Avoid contact with eyes. In case of contact with eyes, rinse thoroughly and consult your veterinarian. If skin irritation occurs or increases, discontinue use and consult your veterinarian.

WARNING: Keep out of the reach of children.

STORAGE AND HANDLING

STORAGE CONDITIONS: Store at room temperature. Do not freeze.

Questions? 1-800-999-0297

Pivetal

Distributed by:

Aspen Veterinary Resources®, LTD.

Liberty, MO 64068

pivetalvet.com

PRINCIPAL DISPLAY PANEL - 8 OUNCE (237 mL) Bottle

Pivetal

NDC 46066-038-90

Suffusion™ 4%

FOR DOGS & CATS

Chlorhexidine Gluconate 4%

ANTISEPTIC SHAMPOO

8 fl oz (237 mL)

ANTIBACTERIAL
ANTIFUNGAL

PRINCIPAL DISPLAY PANEL - 16 OUNCE (473 mL) Bottle

Pivetal

NDC 46066-038-91

Suffusion™ 4%

FOR DOGS & CATS

Chlorhexidine Gluconate 4%

ANTISEPTIC SHAMPOO

16 fl oz (473 mL)

ANTIBACTERIAL
ANTIFUNGAL